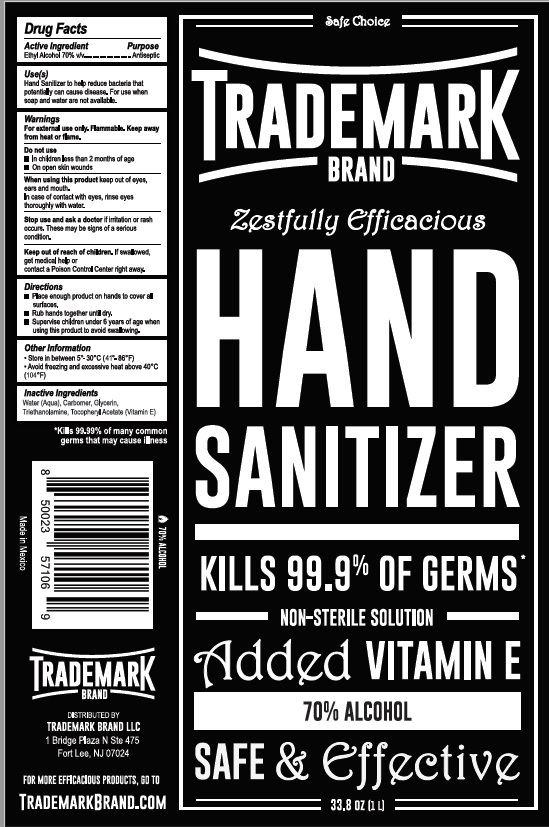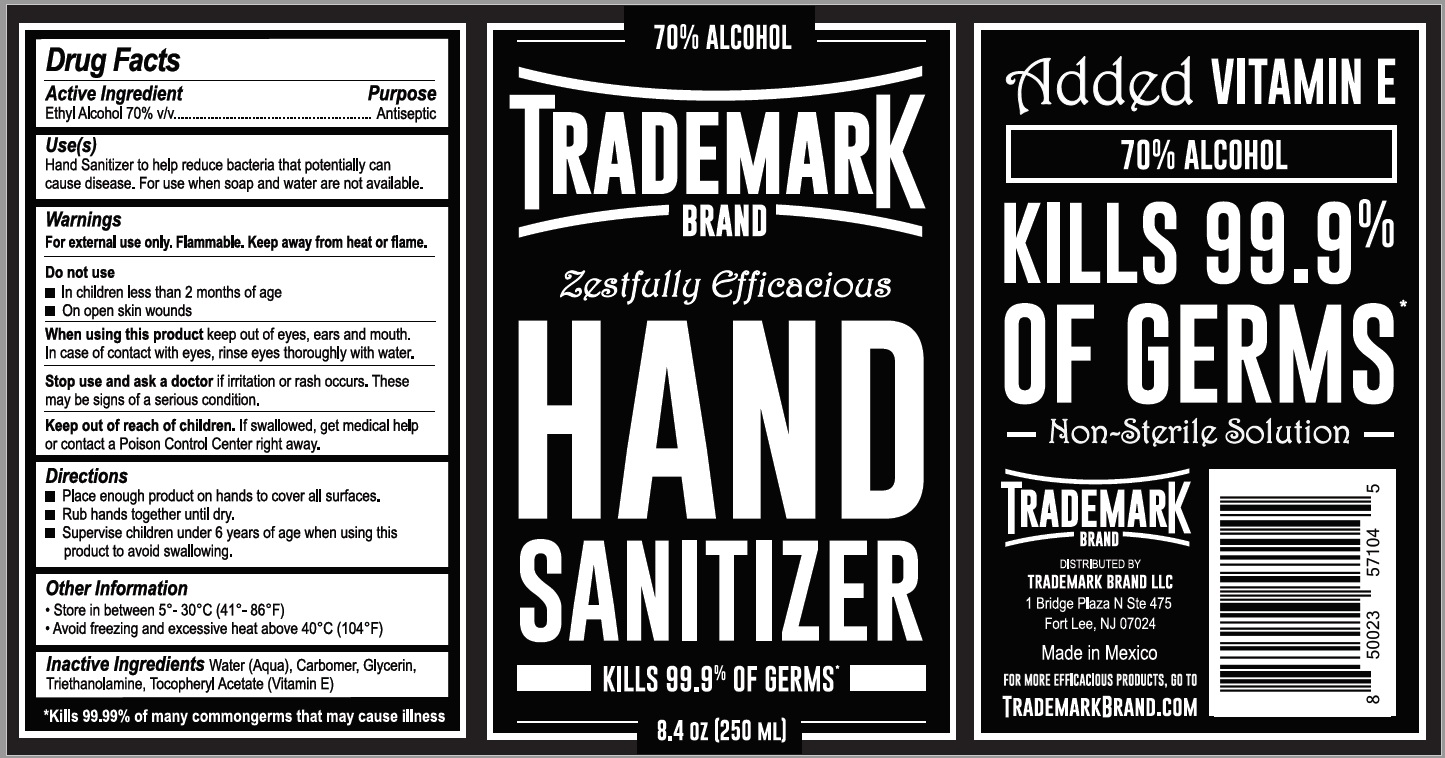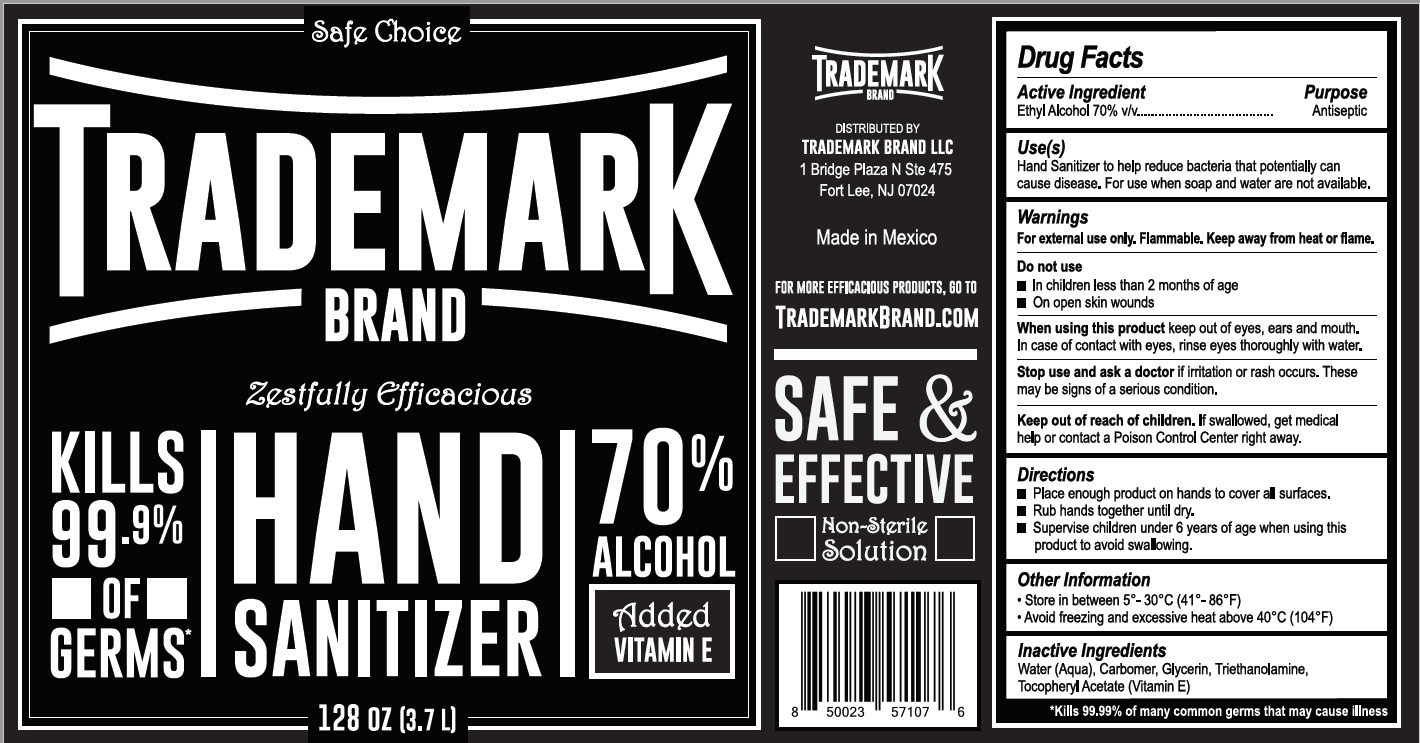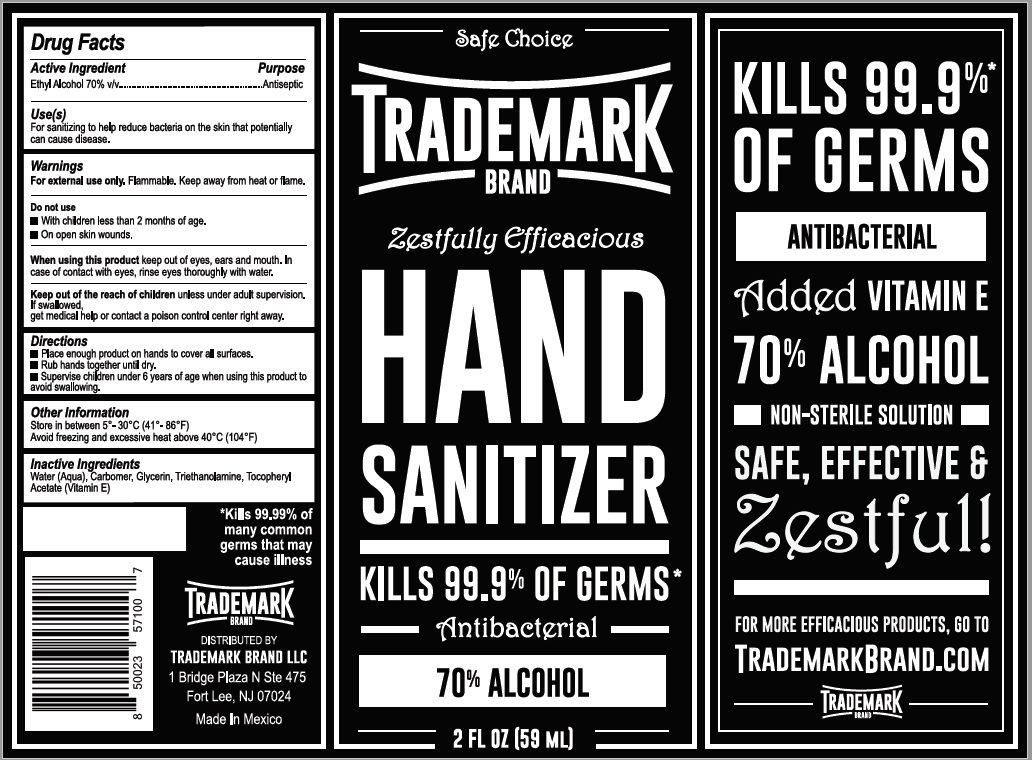 DRUG LABEL: Trademark Hand Sanitizer
NDC: 79337-172 | Form: GEL
Manufacturer: Organikisimo, S.A. de C:V.
Category: otc | Type: HUMAN OTC DRUG LABEL
Date: 20201119

ACTIVE INGREDIENTS: ALCOHOL 70 mL/100 mL
INACTIVE INGREDIENTS: TROLAMINE 0.1 mL/100 mL; GLYCERIN 0.8 mL/100 mL; WATER 28.3 mL/100 mL; POLYACRYLIC ACID (8000 MW) 0.6 mL/100 mL; .ALPHA.-TOCOPHEROL ACETATE 0.15 mL/100 mL

TRADEMARK HAND SANITIZER Alcohol 70%

Active Ingredient(s)

Ethyl Alcohol 70% v/v. Purpose: Antiseptic

Purpose

Antiseptic

Use

For sanitizing to help reduce bacteria on the skin that potentially can cause disease.

Warnings

For external use only. Flammable. Keep away from heat or flame

Do not use

- in children less than 2 months of age
- on open skin wounds

When using this product keep out of eyes, ears, and mouth. In case of contact with eyes, rinse eyes thoroughly with water.
Keep out of reach of children. If swallowed, get medical help or contact a Poison Control Center right away.

Keep out of reach of children. If swallowed, get medical help or contact a Poison Control Center right away.

Directions

- Place enough product on hands to cover all surfaces. Rub hands together until dry.
- Supervise children under 6 years of age when using this product to avoid swallowing.

Other information

- Store between 15-30C (59-86F)
- Avoid freezing and excessive heat above 40C (104F)

Inactive ingredients

Water, Carbomer, Glycerin,Triethanolamine, Tocopheryl Acetate (Vitamin E).

Package Label - TRADEMARK 59 ml NDC:79337-172-01

59 ml NDC:79337-172-01

Package Label - TRADEMARK 250 ml NDC:79337-172-02

250 ml NDC: 79337-172-02

Package Label - TRADEMARK 1000 ml NDC:79337-172-03

1000 ml NDC: 79337-172-03

Package Label - TRADEMARK 3785 ml NDC: 79337-172-04

3785 ml NDC: 79337-172-04